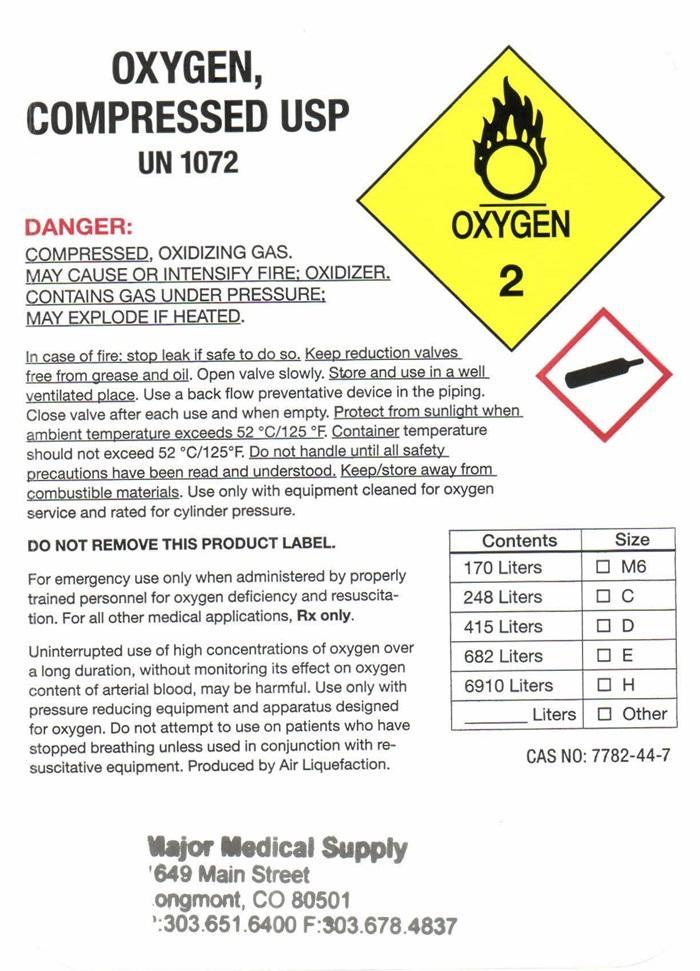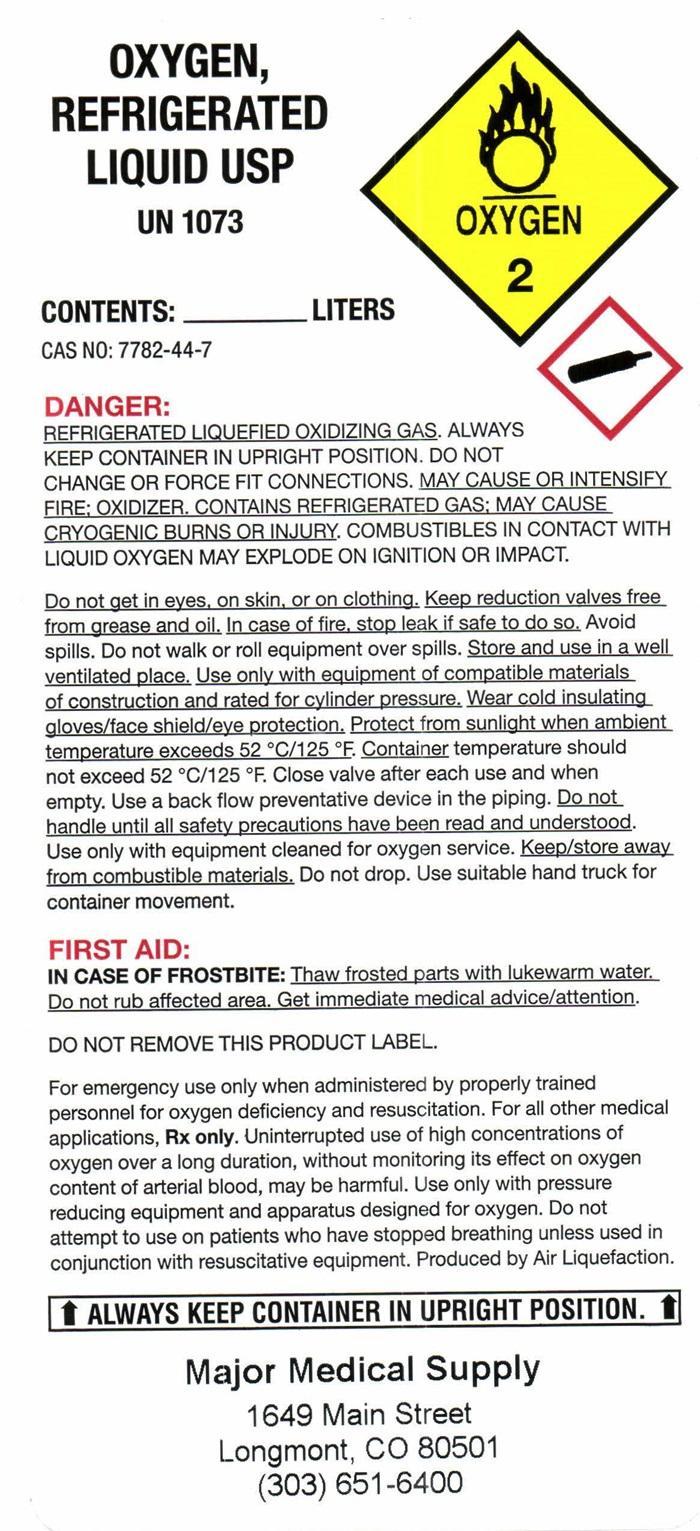 DRUG LABEL: OXYGEN
NDC: 65700-1649 | Form: GAS
Manufacturer: Major Medical Supply LLC
Category: prescription | Type: HUMAN PRESCRIPTION DRUG LABEL
Date: 20191028

ACTIVE INGREDIENTS: OXYGEN 99 L/100 L

Oxygen

OXYGEN COMPRESSED USP Product Label

OXYGEN COMPRESSED USP UN 1072
OXYGEN-2
DANGER:
COMPRESSED, OXIDIZING GAS, MAY CAUSE OR INTENSIFY FIRE; OXIDIZER, CONTAINS GAS UNDER PRESSURE; MAY EXPLODE IF HEATED.
In case of fire: stop leak if safe to do so. Keep reduction valves free from grease and oil. Open valve slowly. Store and use in a well ventilated place. Use a back flow preventive device in the piping. Close valve after after each use and when empty. Protect from sunlight when ambient temperature exceeds 52° C/125° F. Container temperature should not exceed 52° C/125° F. Do not handle until all safety precautions have been read and understood. Keep/store away from combustible materials. Use only with equipment cleaned for oxygen service and rated for cylinder pressure.
DO NOT REMOVE THIS PRODUCT LABEL.
For emergency use only when administered by properly trained personnel for oxygen deficiency and resuscitation. For all other medical applications, Rx only.
Uninterrupted use of high concentrations of oxygen over a long duration, without monitoring its effect on oxygen content of arterial blood, may be harmful. Use only with pressure reducing equipment and apparatus designed for oxygen. Do not attempt to use on patents who have stopped breathing unless used in conjunction with resuscitative equipment. Produced by Air Liquefaction

Contents | Size
170 Liters | M6
248 Liters | C
415 Liters | D
682 Liters | E
6910 Liters | H
____________ Liters | Other

CAS NO: 7782-44-7
Major Medical Supply
1649 Main Street
Longmont, CO 80501
(303) 651-6400

OXYGEN REFRIGERATED LIQUID USP Product Label

OXYGEN REFRIGERATED LIQUID USP UN 1073

OXYGEN 2

CONTENTS: ___________________ LITERS

CAS NO:7782-44-7

DANGER:

REFRIGERATED LIQUEFIED OXIDIZING GAS. ALWAYS KEEP CONTAINER IN UPRIGHT POSITION. DO NOT CHANGE OR FORCE FIT CONNECTIONS. MAY CAUSE OR INTENSIFY FIRE: OXIDIZER. CONTAINS REFRIGERATED GAS: MAY CAUSE CRYOGENIC BURNS OR INJURY. COMBUSTIBLES IN CONTACT WITH LIQUID OXYGEN MAY EXPLODE ON IGNITION OR IMPACT.

Do not get into eyes, on skin, or on clothing. Keep reduction valves free from grease and oil. In case of fire, stop leak if safe to do so. Avoid spills. Do not walk or roll equipment over spills. Store and use in a well ventilated place. use only with equipment of compatible materials of construction and rated for cylinder pressure. Wear cold insulating gloves/face shield/eye protection. Protect from sunlight when ambient temperature exceeds 52° C/125° F. Container temperature should not exceed 52° C/125° F. Close valve after each use and when empty. Use a back flow preventive device in the pipping. Do not handle until all safety precautions have been read and understood. Use only with equipment cleaned for oxygen service. Keep/store away from combustible materials. Do not drop. Use suitable hand truck for container movement.

FIRST AID:

IN CASE OF FROSTBITE: Thaw frosted parts with lukewarm water. Do not rub affected area. Get immediate medical advise/attention.

DO NOT REMOVE THIS PRODUCT LABEL

For emergency use only when administered by properly trained personnel for oxygen deficiency and resuscitation. For all other medical applications, Rx only. Uninterrupted use of high concentrations of oxygen over a long duration, without monitoring its effect on oxygen content of arterial blood, may be harmful. Use only with pressure reducing equipment and apparatus designed for oxygen. Do not attempt to use on patients who have stopped breathing unless used in conjunction with resuscitative equipment. Produced by Air Liquefaction.

ALWAYS KEEP CONTAINER IN UPRIGHT POSITION

Major Medical Supply
1649 Main Street
Longmont, CO 80501
(303) 651-6400